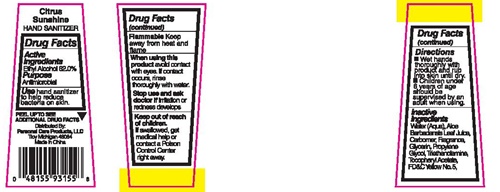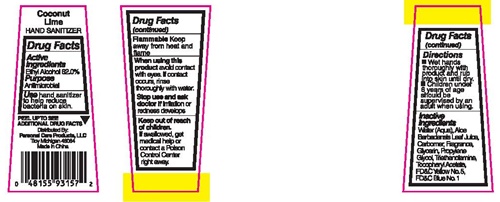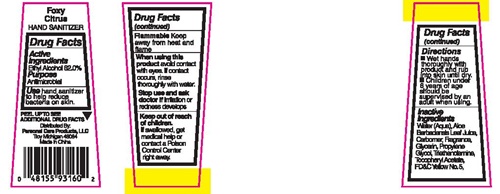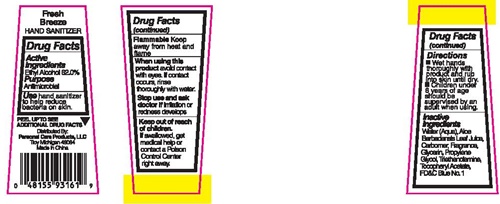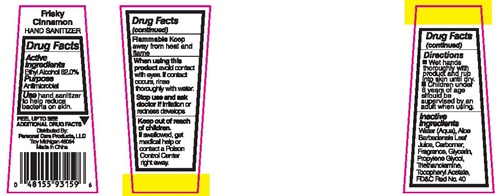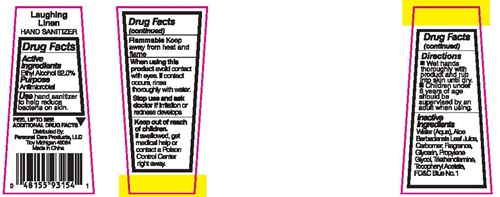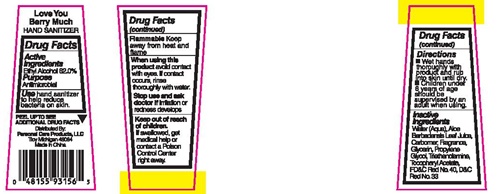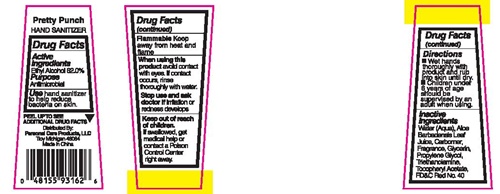 DRUG LABEL: Laughing Linen
NDC: 29500-9354 | Form: LIQUID
Manufacturer: Personal Care Products LLC
Category: otc | Type: HUMAN OTC DRUG LABEL
Date: 20170303

ACTIVE INGREDIENTS: ALCOHOL 26.36 g/44 mL
INACTIVE INGREDIENTS: WATER; ALOE VERA LEAF; CARBOXYPOLYMETHYLENE; GLYCERIN; PROPYLENE GLYCOL; TROLAMINE; .ALPHA.-TOCOPHEROL ACETATE; FD&C BLUE NO. 1

Laughing Linen - 9354
Citrus Sunshine - 9355
Love You Berry Much - 9356
Coconut Lime - 9357
Frisky Cinnamon - 9359
Foxy Citrus - 9360
Fresh Breeze - 9361
Pretty Punch - 9362

Drug Facts Active ingredients

Ethyl Alcohol 62.0%

Purpose

Antimicrobial

Use

hand sanitizer to help reduce bacteria on skin.

Flammable

Keep away from heat and flame

When using this product

avoid contact with eyes. I contact occurs, rinse thoroughly with water.

Stop use and ask a doctor if

irritation or redness develops.

Keep out of reach of children.

If swallowed, get medical help or contact a Poison Control Center right awawy.

Directions

- Wet hands thoroughly with product and rub into skin until dry.
- Children under 6 years of age should be supervised by an adult when using.

Inactive ingredients

Water (Aqua), Aloe Barbadensis Leaf Juice, Carbomer, Fragrance, Glycerin, Propylene Glycol, Triethanolamine, Tocopheryl Acetate, FD&C Blue No.1, FD&C Yellow No. 5, FD&C Red No. 40, D&C Red No. 33

Laughing Linen - 9354 Citrus Sunshine - 9355 Love You Berry Much - 9356 Coconut Lime - 9357 Frisky Cinnamon - 9359 Foxy Citrus - 9360 Fresh Breeze - 9361 Pretty Punch - 9362 Product Labels

PEEL UP TO SEE ADDITIONAL DRUG FACTS

Distributed By:
Personal Care Products, LLC
Troy, Michigan 48084
Made in China

Laughing Linen - 9354

Citrus Sunshine - 9355

Love You Berry Much - 9356

Coconut Lime - 9357

Frisky Cinnamon - 9359

Foxy Citrus - 9360

Fresh Breeze - 9361

Pretty Punch - 9362